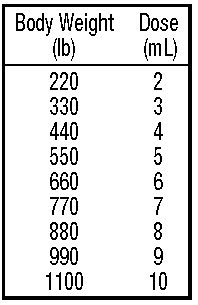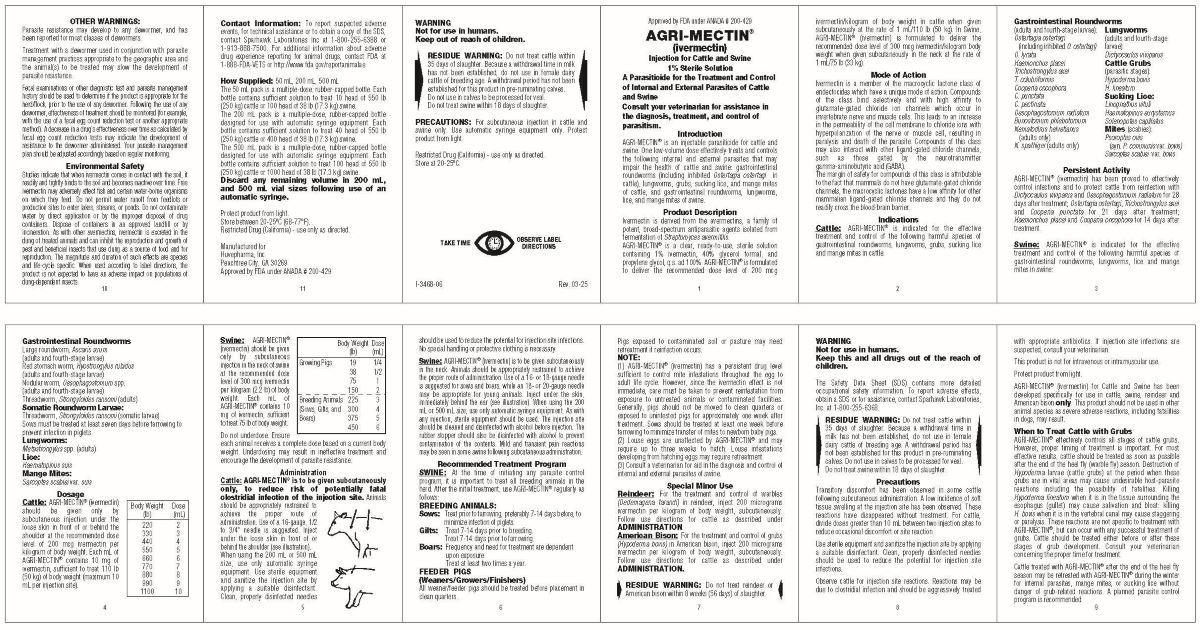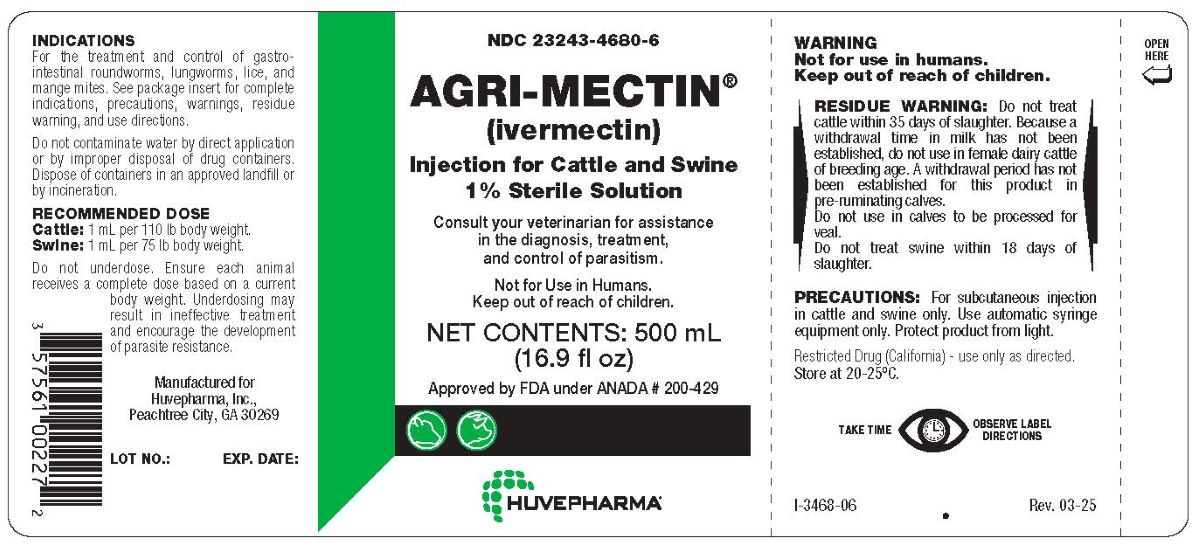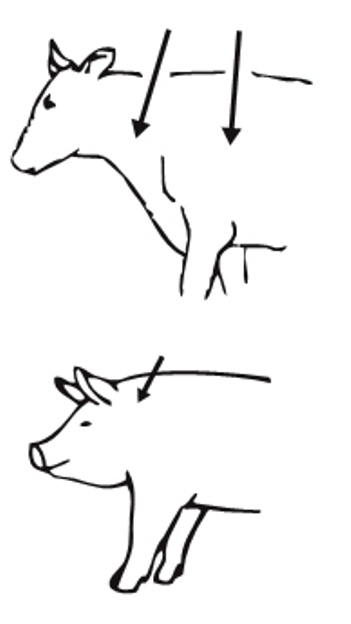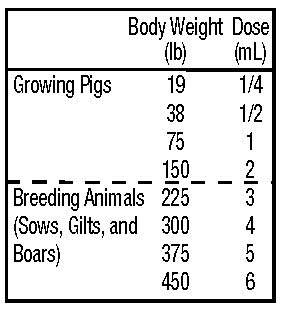 DRUG LABEL: AGRI-MECTIN
NDC: 23243-4680 | Form: INJECTION
Manufacturer: Huvepharms, Inc
Category: animal | Type: OTC ANIMAL DRUG LABEL
Date: 20250428

ACTIVE INGREDIENTS: IVERMECTIN 10 mg/1 mL
INACTIVE INGREDIENTS: GLYCEROL FORMAL, .ALPHA.,.ALPHA'

AGRI-MECTIN (ivermectin)

DESCRIPTION

Approved by FDA under ANADA # 200-429
Injection for Cattle and Swine
1% Sterile Solution
A Parasiticide for the Treatment and Control of Internal and External Parasites of Cattle and Swine
Consult your veterinarian for assistance in the diagnosis, treatment, and control of parasitism.

DESCRIPTION

Introduction
AGRI-MECTIN® is an injectable parasiticide for cattle and swine. One low-volume dose effectively treats and controls the following internal and external parasites that may impair the health of cattle and swine: gastrointestinal roundworms (including inhibited Ostertagia ostertagi in cattle), lungworms, grubs, sucking lice, and mange mites of cattle; and gastrointestinal roundworms, lungworms, lice, and mange mites in swine.
Product Description
Ivermectin is derived from the avermectins, a family of potent, broad-spectrum antiparasitic agents isolated from fermentation of Streptomyces avermitilis.AGRI-MECTIN® Injection is a clear, ready-to-use, sterile solution containing 1% ivermectin, 40% glycerol formal, and propylene glycol, q.s. ad 100%. AGRI-MECTIN® Injection is formulated to deliver the recommended dose level of 200 mcg ivermectin/kilogram of body weight in cattle when given subcutaneously at the rate of 1 mL/110 lb (50 kg). In Swine, AGRI-MECTIN Injection is formulated to deliver the recommended dose level of 300 mcg ivermectin/kilogram body weight when given subcutaneously in the neck at the rate of 1 mL/75 lbs (33 kg).

Mode of Action

Ivermectin is a member of the macrocyclic lactone class of endectocides which have a unique mode of action. Compounds of the class bind selectively and with high affinity to glutamate-gated chloride ion channels which occur in invertebrate nerve and muscle cells. This leads to an increase in the permeability of the cell membrane to chloride ions with hyperpolarization of the nerve or muscle cell, resulting in paralysis and death of the parasite. Compounds of this class may also interact with other ligand-gated chloride channels, such as those gated by the neurotransmitter gamma-aminobutyric acid (GABA)

The margin of safety for compounds of this class is attributable to the fact that mammals do not have glutamate-gated chloride channels, the macrocyclic lactones have a low affinity for other mammalian ligand-gated chloride channels and they do not readily cross the blood-brain barrier.

Indications

Cattle: AGRI-MECTIN® Injection is indicated for the effective treatment and control of the following harmful species of gastrointestinal roundworms, lungworms, grubs, sucking lice and mange mites in cattle:
Gastrointestinal Roundworms(adults and fourth-stage larvae):
Ostertagia ostertagi (Including inhibited O. ostertagi)
O. lyrata
Haemonchus placei
Trichostrongylus axei
T. colubriformis
Cooperia oncophora
C. punctata
C. pectinata
Oesophagostomum radiatum
Bunostomum phlebotomum
Nematodirus helvetianus(adults only)
N. spathiger (adults only)
Lungworms
(adults and fourth-stage larvae):
Dictyocaulus viviparus

Cattle Grubs

(parasitic stages):
Hypoderma bovis
H. lineatum

Sucking Lice:
Linognathus vituli
Haematopinus eurysternus
Solenopotes capillatus

Mites (scabies):
Psoroptes ovis

(syn. P. communis var. bovis)
Sarcoptes scabiei var. bovis

Persistent Activity

AGRI-MECTIN® Injection has been proved to effectively control infections and to protect cattle from reinfection with Dictyocaulus viviparus and Oesophagostomum radiatum for 28 days after treatment; Ostertagia ostertagi, Trichostrongylus axei and Cooperia punctata for 21 days after treatment; Haemonchus placei and Cooperia oncophora for 14 days after treatment.

Swine: AGRI-MECTIN® Injection is indicated for the effective treatment and control of the following harmful species of gastrointestinal roundworms, lungworms, lice and mange mites in swine:

Gastrointestinal roundworms
Large roundworm, Ascaris suum(adults and fourth-stage larvae)
Red stomach worm, Hyostrongylus rubidus
(adults and fourth-stage larvae)
Nodular worm, Oesophagostomum spp.
(adults and fourth-stage larvae)
Threadworm, Strongyloides ransomi (adults)
Somatic Roundworm Larvae:
Threadworm, Strongyloides ransomi (somatic larvae)
Sows must be treated at least seven days before farrowing to prevent infection in piglets.
Lungworm:

Metastrongylus spp. (adults)
Lice:

Haematopinus suis

Mange Mites: Sarcoptes scabiei var. suis

Dosage

Cattle: AGRI-MECTIN® should be given only by subcutaneous injection under the loose skin in front of or behind the shoulder at the recommended dose level of 200 mcg ivermectin per kilogram of body weight. Each mL of AGRI-MECTIN® contains 10 mg of ivermectin, sufficient to treat 110 lb (50 kg) of body weight (maximum 10 mL per injection site.).

Swine: AGRI-MECTIN® should be given only by subcutaneous injection in the neck of swine at the recommended dose level of 300 mcg ivermectin per kilogram (2.2 lb) of body weight. Each mL of AGRI-MECTIN® contains 10 mg of ivermectin, sufficient to treat 75 lb of body weight.

Do not underdose. Ensure each animal receives a complete dose based on a current body weight. Underdosing may result in ineffective treatment and encourage the development of parasite resistance.

Administration

Cattle: AGRI-MECTIN® Injection is to be given subcutaneously only, to reduce risk of potentially fatal clostridial infection of the injection site.Animals should be appropriately restrained to achieve the proper route of administration. Use of a 16-gauge, 1/2 to 3/4" needle is suggested. Inject under the loose skin in front of or behind the shoulder (see illustration). When using the 200 mL or 500 mL size, use only automatic syringe equipment. Use sterile equipment and sanitize the injection site by applying a suitable disinfectant. Clean, properly disinfected needles should be used to reduce the potential for injection site infections. No special handling or protective clothing is necessary.

Swine: AGRI-MECTIN® Injection is to be given subcutaneously in the neck. Animals should be appropriately restrained to achieve the proper route of administration. Use of a 16- or 18-gauge needle is suggested for sows and boars, while an 18- or 20-gauge needle may be appropriate for young animals. Inject under the skin, immediately behind the ear (see illustration). When using the 200 mL or 500 mL size, use only automatic syringe equipment. As with any injection, sterile equipment should be used. The injection site should be cleaned and disinfected with alcohol before injection. The rubber stopper should also be disinfected with alcohol to prevent contamination of the contents. Mild and transient pain reactions may be seen in some swine following subcutaneous administration.

Recommended Treatment Program

SWINE: At the time of initiating any parasite control program, it is important to treat all breeding animals in the herd. After the initial treatment, use AGRI-MECTIN® Injection regularly as follows:
BREEDING ANIMALS:
Sows: Treat prior to farrowing, preferably 7 - 14 days before, to minimize infection of piglets.
Gilts: Treat 7 - 14 days prior to breeding.
Treat 7 - 14 days prior to farrowing.
Boars: Frequency and need for treatment are dependent upon exposure. Treat at least two times a year.
FEEDER PIGS
(Weaners/Growers/Finishers)
All weaner/feeder pigs should be treated before placement in clean quarters.
Pigs exposed to contaminated soil or pasture may need retreatment if reinfection occurs.
NOTE:
(1) AGRI-MECTIN® Injection has a persistent drug level sufficient to control mite infestations throughout the egg to adult life cycle. However, since the ivermectin effect is not immediate, care must be taken to prevent reinfestation from exposure to untreated animals or contaminated facilities. Generally, pigs should not be moved to clean quarters or exposed to uninfested pigs for approximately one week after treatment. Sows should be treated at least one week before farrowing to minimize transfer of mites to newborn baby pigs.
(2) Louse eggs are unaffected by AGRI-MECTIN Injection and may require up to three weeks to hatch. Louse infestations developing from hatching eggs may require retreatment.
(3) Consult a veterinarian for aid in the diagnosis and control of internal and external parasites of swine.

Special Minor Use
Reindeer: For the treatment and control of warbles (Oedemagena tarandi) in reindeer, inject 200 micrograms ivermectin per kilogram of body weight, subcutaneously. Follow use directions for cattle as described under ADMINISTRATION.
American Bison: For the treatment and control of grubs (Hypoderma bovis) in American bison, inject 200 micrograms ivermectin per kilogram of body weight, subcutaneously. Follow use directions for cattle as described under ADMINISTRATION.

WARNINGS

RESIDUE WARNING: Do not treat reindeer or American bison within 8 weeks (56 days) of slaughter.

WARNING

Not for use in humans.

Keep this and all drugs out of the reach of children.

The Safety Data Sheet (SDS) contains more detailed occupational safety information. To report adverse effects, obtain a SDS or for assistance, contact Huvepharma, Inc. at 1-877-994-4883.

RESIDUE WARNING: Do not treat cattle within 35 days of slaughter. Because a withdrawal time in milk has not been established, do not use in female dairy cattle of breeding age. A withdrawal period has not been established for this product in pre-ruminating calves. Do not use in calves to be processed for veal. Do not treat swine within 18 days of slaughter.

Precautions

Transitory discomfort has been observed in some cattle following subcutaneous administration. A low incidence of soft tissue swelling at the injection site has been observed. These reactions have disappeared without treatment. For cattle, divide doses greater than 10 mL between two injection sites to reduce occasional discomfort or site reaction.

Use sterile equipment and sanitize the injection site by applying a suitable disinfectant. Clean, properly disinfected needles should be used to reduce the potential for injection site infection.

Observe cattle for injection site reactions. Reactions may be due to clostridial infection and should be aggressively treated with appropriate antibiotics. If injection site infections are suspected, consult your veterinarian.

This product is not for intravenous or intramuscular use.

Protect product from light.

AGRI-MECTIN® Injection for Cattle and Swine has been developed specifically for use in cattle, swine, reindeer and American bison only. This product should not be used in other animal species as severe adverse reactions, including fatalities in dogs may result.

When to Treat Cattle with Grubs
AGRI-MECTIN® effectively controls all stages of cattle grubs. However, proper timing of treatment is important. For most effective results, cattle should be treated as soon as possible after the end of the heel fly (warble fly) season. Destruction of Hypoderma larvae (cattle grubs) at the period when these grubs are in vital areas may cause undesirable host-parasite reactions including the possibility of fatalities. Killing Hypoderma lineatum when it is in the tissue surrounding the esophagus (gullet) may cause salivation and bloat.: Killing H. bovis when it is in the vertebral canal may cause staggering or paralysis. These reactions are not specific to treatment with AGRI-MECTIN®, but can occur with any successful treatment of grubs. Cattle should be treated either before or after these stages of grub development. Consult your veterinarian concerning the proper time for treatment. Cattle treated with AGRI-MECTIN® after the end of the heel fly season may be retreated with AGRI-MECTIN during the winter for internal parasites, mange mites, or sucking lice without danger of grub-related reactions. A planned parasite control program is recommended.

OTHER WARNINGS:

Parasite resistance may develop to any dewormer, and has been reported for most classes of dewormers.
Treatment with a dewormer used in conjunction with parasite management practices appropriate to the geographic area and the animal(s) to be treated may slow the development of parasite resistance.
Fecal examinations or other diagnostic test and parasite management history should be used to determine if the product is appropriate for the herd/ﬂock, prior to the use of any dewormer. Following the use of any dewormer, effectiveness of treatment should be monitored (for example, with the use of a fecal egg count reduction test or another appropriate method). A decrease in a drug’s effectiveness over time as calculated by fecal egg count reduction tests may indicate the development of resistance to the dewormer administered. Your parasite management plan should be adjusted accordingly based on regular monitoring.

Environmental Safety

Studies indicate that when ivermectin comes in contact with the soil, it readily and tightly binds to the soil and becomes inactive over time. Free ivermectin may adversely affect fish and certain water-borne organisms on which they feed. Do not permit water runoff from feedlots or production sites to enter lakes, streams, or ponds. Do not contaminate water by direct application or by the improper disposal of drug containers. Dispose of containers in an approved landfill or by incineration.
As with other avermectins, ivermectin is excreted in the dung of treated animals and can inhibit the reproduction and growth of pest and beneficial insects that use dung as a source of food and for reproduction. The magnitude and duration of such effects are species and lifestyle specific. When used according to label directions, the product is not expected to have an adverse impact on populations of dung-dependent insects.

Contact Information

To report suspected adverse events, for technical assistance or to obtain a copy of the SDS, contact Sparhawk Laboratories Inc at 1-800-255-6388 or 1-913-888-7500. For additional information about adverse drug experience reporting for animal drugs, contact FDA at 1-888-FDA-VETS or http://www.fda.gov/reportanimalae

How Supplied

50 mL, 200 mL, 500 mL
The 50 mL pack is a multiple-dose, rubber-capped bottle. Each bottle contains sufficient solution to treat 10 head of 550 lb (250 kg) cattle or 100 head of 38 lb (17.3 kg) swine. The 200 mL pack is a multiple-dose, rubber-capped bottle designed for use with automatic syringe equipment. Each bottle contains sufficient solution to treat 40 head of 550 lb (250 kg) cattle or 400 head of 38 lb (17.3 kg) swine. The 500 mL pack is a multiple-dose, rubber-capped bottle designed for use with automatic syringe equipment. Each bottle contains sufficient solution to treat 100 head of 550 lb (250 kg) cattle or 1000 head of 38 lb (17.3 kg) swine.

STORAGE AND HANDLING

Protect product from light. Store at 20-25ºC.
Restricted Drug (California) - use only as directed.
The 50 mL pack is a multiple-dose, rubber-capped bottle. Each bottle contains sufﬁcient solution to treat 10 head of 550 lb (250 kg) cattle or 100 head of 38 lb (17.3 kg) swine.
The 250 mL pack is a multiple-dose, rubber-capped bottle designed for use with automatic syringe equipment. Each bottle contains sufﬁcient solution to treat 50 head of 550 lb (250 kg) cattle or 500 head of 38 lb (17.3 kg) swine.
The 500 mL pack is a multiple-dose, rubber-capped bottle designed for use with automatic syringe equipment. Each bottle contains sufﬁcient solution to treat 100 head of 550 lb (250 kg) cattle or 1000 head of 38 lb (17.3 kg) swine. Discard any remaining volume in 200 mL, and 500 mL vial sizes following use of an automatic syringe.

Discard any remaining volume in 200 mL, and 500 mL vial sizes following use of an automatic syringe.

Manufactured for Huvepharma, Inc. Peachtree City, GA 30269

Approved by FDA under ANADA # 200-429

PACKAGE LABEL

NDC 23243-4680-6
AGRI-MECTIN®

(ivermectin)

Injection for Cattle and Swine

1% Sterile Solution

Consult your veterinarian for assistance
in the diagnosis, treatment,
and control of parasitism.

Approved by FDA under ANADA # 200-429

NET CONTENTS: 500 mL
(16.9 ﬂ oz)